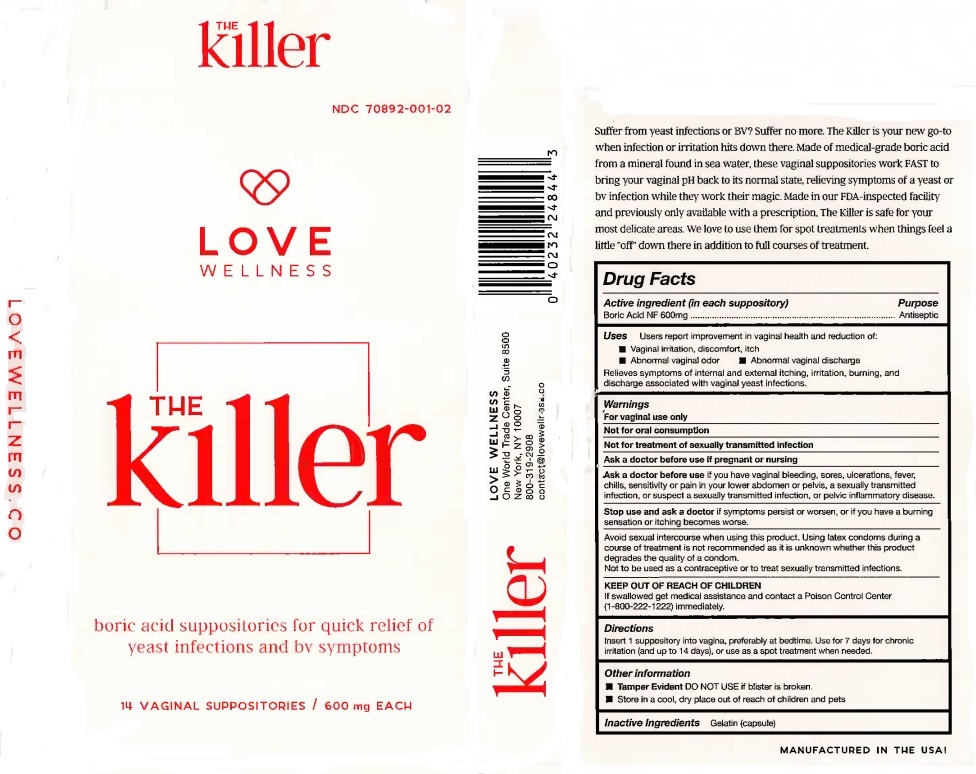 DRUG LABEL: The Killer
NDC: 70892-001 | Form: SUPPOSITORY
Manufacturer: Ogilvie Brands Inc DBA Love Wellness
Category: homeopathic | Type: HUMAN OTC DRUG LABEL
Date: 20191230

ACTIVE INGREDIENTS: BORIC ACID 600 mg/1 1
INACTIVE INGREDIENTS: GELATIN

The Killer

Active ingredient (in each suppository)

Boric Acid NF 600mg

Uses

Users report improvement in vaginal health and reduction of:

• Vaginal irritation, discomfort, itch

• Abnormal vaginal odor

• Abnormal vaginal discharges

Relieves symptoms of internal and external itching, irritation, burning, and discharge associated with vaginal yeast infections.

Warnings

For vaginal use only

Not for oral consumption

Not for treatment of sexually transmitted infection

Ask a doctor before use if pregnant or nursing

Ask a doctor before use if you have vaginal bleeding, sores, ulcerations, fever, chills, sensitivity or pain in your lower abdomen or pelvis, a sexually transmitted infection, or suspect a sexually transmitted infection, or pelvic inflammatory disease.

Stop use and ask a doctor if symptoms persist or worsen, or if you have a burning sensation or itching becomes worse.

Avoid sexual intercourse when using this product. Using latex condoms during a course of treatment is not reccommended as it is unknown whether this product degrades the quality of a condom.

Not to be used as a contraceptive or to treat sexually transmitted infections.

KEEP OUT OF REACH OF CHILDREN

If swallowed get medical assistance and contact a Poison Control Center

(1-800-222-1222) immediately.

KEEP OUT OF REACH OF CHILDREN

If swallowed get medical assistance and contact a Poison Control Center

(1-800-222-1222) immediately.

Directions

Insert 1 suppository into vagina, preferably at bedtime. Use for 7 days of chronic irritation (and up to 14 days), or use as a spot treatment when needed.

Other information• Tamper Evident DO NOT USE if blister is broken.

• Store in a cool, dry place out of reach of children and pets

Inactive Ingredients Gelatin (Capsule)

QUESTIONS

LOVE WELLNESS

One World Trade Center, Suite 8500

New York, NY 10007

800-319-2908

contact@lovewell.co

PACKAGE LABEL

THE killer

NDC 70892-001-02

LOVE WELLNESS

THE Killer

boric acid suppositories for quick relief of yeast infections and by symptoms

14 VAGINAL SUPPOSITORIES / 600 mg EACH

Purpose...Antiseptic

Suffer from yeast infections or BV? Suffer no more. The Killer is your new go-to when infection or irritation hits down there. Made of medical-grade boric acid from a mineral found in sea water, these vaginal suppositories work FAST to bring your vaginal pH back to its normal state, relieving symptoms of a yeast or bv infection while they work their magic. Made on our FDA inspected facility and previously only avaiable with a prescription. The Killer is safe for your delicate areas. We lose to use them for spot treatments when things feel a little "off" down there in addition to full courses of treatment.